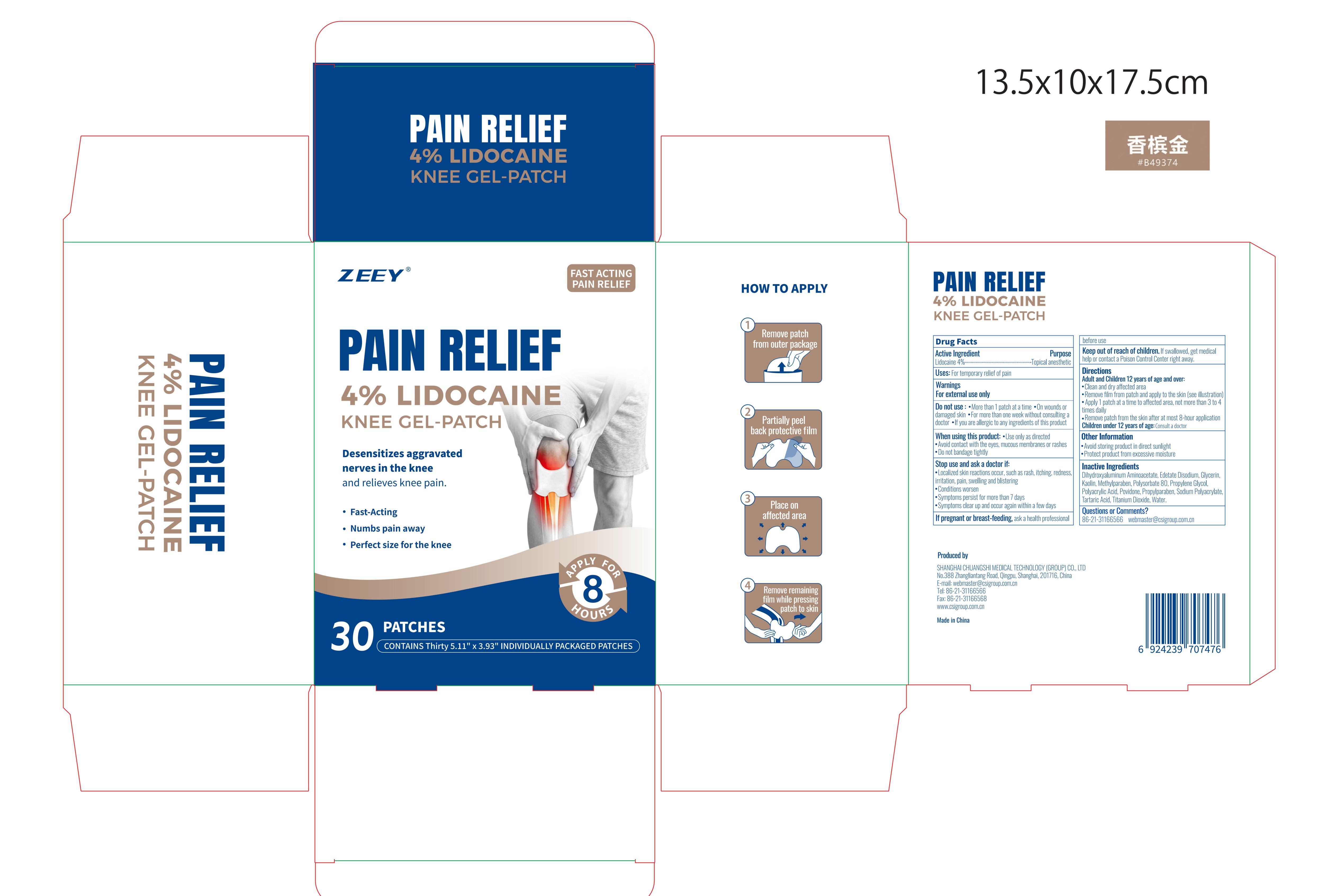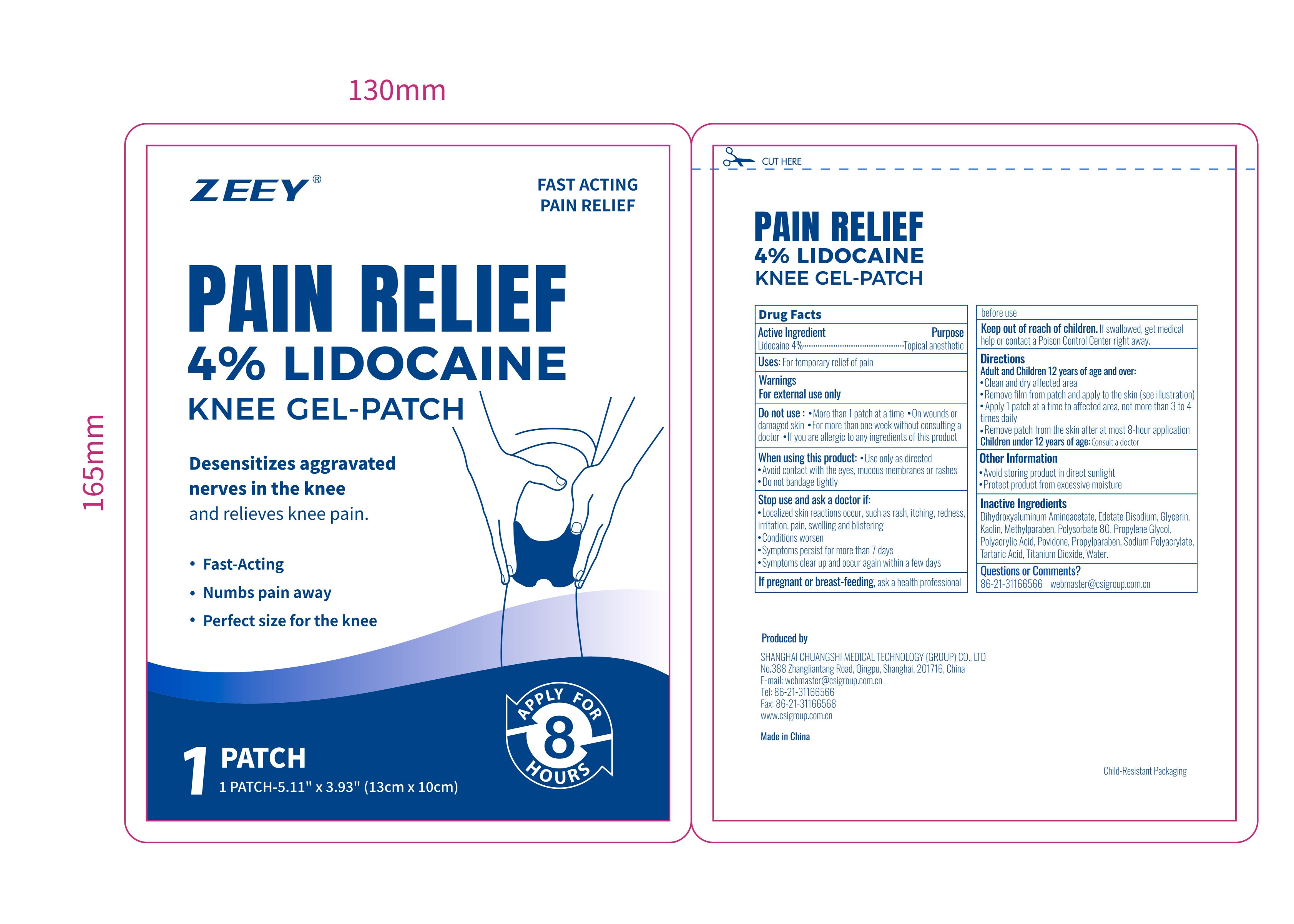 DRUG LABEL: Pain Relief
NDC: 73557-189 | Form: PATCH
Manufacturer: Shanghai Chuangshi Medical Technology (Group) Co., Ltd.
Category: otc | Type: HUMAN OTC DRUG LABEL
Date: 20251110

ACTIVE INGREDIENTS: LIDOCAINE 0.04 g/1 g
INACTIVE INGREDIENTS: POLYSORBATE 80; GLYCERIN; POVIDONE K90; METHYLPARABEN; PROPYLPARABEN; EDETATE DISODIUM; KAOLIN; TARTARIC ACID; WATER; PROPYLENE GLYCOL; POLYACRYLIC ACID (250000 MW); SODIUM POLYACRYLATE (2500000 MW); TITANIUM DIOXIDE; DIHYDROXYALUMINUM AMINOACETATE ANHYDROUS

Zeey, Pain Relief

Active ingredient

Lidocaine 4% ...... Purpose: Topical Anesthetic

Purpose

Topical Anesthetic

Uses

For temporary relief of pain

Warnings

For external use only

Ask a doctor if:

- localized skin reactions occur, such as rash, itching, redness, irritation, pain, swelling and blistering
- Conditions worsen
- Symptoms persists for more than 7 days
- Symptoms clear up and occur again within a few days

When using this product

- Use only as directed
- Avoid contact with the eyes, mucous membranes or rashed
- Do not bandage tightly

Do not use

- More than 1 patch at a time
- On wounds or damaged skin
- For more than one week without consulting a doctor
- If you are allergic to any ingredients of this product

Stop use if:

- localized skin reactions occur, such as rash, itching, redness, irritation, pain, swelling and blistering
- Conditions worsen
- Symptoms persists for more than 7 days
- Symptoms clear up and occur again within a few days

Pregnancy or breast feeding

If pregnant or breastfeeding, ask a health professional before use

Keep out of reach of children. If swallowed, get medical help or contact a Poison Control Center right away.

Directions

Adult and Children 12 years of age and over:

- Clean and dry affected area
- Remove film from patch and apply to the skin (see illustration)
- Apply 1 patch at a time to affected area, not more than 3 to 4 times daily
- Remove patch from the skin after at most 8-hour application

Children under 12 years of age: Consult a doctor

Dosage forms & strengths

This is a strip, patch dosage form.

The active ingredient strength is 4% w/w.

One patch one time, no more than 8 hours one time.

Inactive ingredients

Dihydroxyaluminum Aminoacetate, Edetate Disodium, Glycerin,
Kaolin, Methylparaben, Polysorbate 80, Propylene Glycol,
Polyacrylic Acid, Povidone, Propylparaben, Sodium Polyacrylate,
Tartaric Acid, Titanium Dioxide, Water.

Questions or Comments?

86-21-31166566 webmaster@csigroup.com.cn

Other information

- Avoid storing product in direct sunlight
- Protect product from excessive moisture